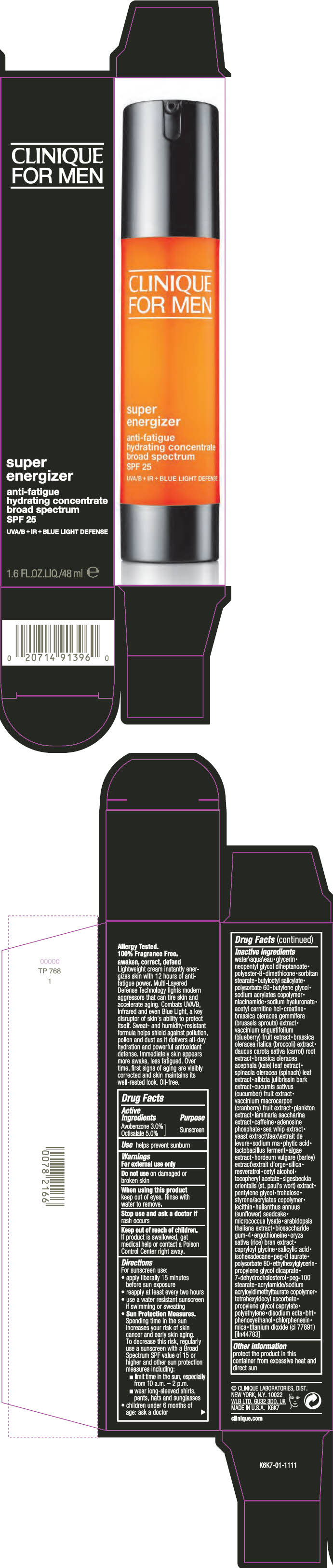 DRUG LABEL: CLINIQUE FOR MEN SUPER ENGERGIZER ANTI -FATIGUE HYDRATING Concentrate BROAD SPECTRUM SPF 25
NDC: 49527-063 | Form: CREAM
Manufacturer: CLINIQUE LABORATORIES LLC
Category: otc | Type: HUMAN OTC DRUG LABEL
Date: 20231013

ACTIVE INGREDIENTS: AVOBENZONE 30 mg/1 mL; OCTISALATE 50 mg/1 mL
INACTIVE INGREDIENTS: CARROT; KALE; SPINACH; CUCUMBER; CRANBERRY; SACCHARINA LATISSIMA; CAFFEINE; ADENOSINE PHOSPHATE; PSEUDOPTEROGORGIA ELISABETHAE; YEAST, UNSPECIFIED; FYTIC ACID; LIMOSILACTOBACILLUS REUTERI; BARLEY; SILICON DIOXIDE; RESVERATROL; CETYL ALCOHOL; .ALPHA.-TOCOPHEROL ACETATE; PENTYLENE GLYCOL; TREHALOSE; HELIANTHUS ANNUUS SEEDCAKE; ARABIDOPSIS THALIANA WHOLE; BIOSACCHARIDE GUM-4; ERGOTHIONEINE; WHITE RICE; CAPRYLOYL GLYCINE; SALICYLIC ACID; ISOHEXADECANE; PEG-8 LAURATE; POLYSORBATE 80; ETHYLHEXYLGLYCERIN; PROPYLENE GLYCOL DICAPRATE; 7-DEHYDROCHOLESTEROL; PEG-100 STEARATE; TETRAHEXYLDECYL ASCORBATE; PROPYLENE GLYCOL MONOCAPRATE; HIGH DENSITY POLYETHYLENE; WATER; GLYCERIN; NEOPENTYL GLYCOL DIHEPTANOATE; POLYESTER-8 (1400 MW, CYANODIPHENYLPROPENOYL CAPPED); DIMETHICONE; SORBITAN MONOSTEARATE; BUTYLOCTYL SALICYLATE; POLYSORBATE 60; BUTYLENE GLYCOL; NIACINAMIDE; HYALURONATE SODIUM; LEVACECARNINE HYDROCHLORIDE; CREATINE; BRUSSELS SPROUT; BLUEBERRY; BROCCOLI; EDETATE DISODIUM ANHYDROUS; BUTYLATED HYDROXYTOLUENE; PHENOXYETHANOL; CHLORPHENESIN; MICA; TITANIUM DIOXIDE

CLINIQUE FOR MEN SUPER ENGERGIZER ANTI -FATIGUE HYDRATING CONCENTRATE BROAD SPECTRUM SPF 25

Drug Facts

Active Ingredients

Avobenzone 3.0%
Octisalate 5.0%

Purpose

Sunscreen

Use

helps prevent sunburn

Warnings

For external use only

Do not use on damaged or broken skin

When using this product keep out of eyes. Rinse with water to remove.

Stop use and ask a doctor if rash occurs

Keep out of reach of children. If product is swallowed, get medical help or contact a Posion Control Center right away.

Directions

For sunscreen use:

- apply liberally 15 minutes before sun exposure
- reapply at least every two hours
- use a water resistant sunscreen if swimming or sweating
- Sun Protection Measures. Spending time in the sun increases your risk of skin cancer and early skin aging. To decrease this risk, regularly use a sunscreen with a Broad Spectrum SPF value of 15 or higher and other sun protection measures including:
  - limit time in the sun, especially from 10 a.m. – 2 p.m.
  - wear long-sleeved shirts, pants, hats and sunglasses
- children under 6 months of age: ask a doctor

Inactive ingredients

water\aqua\eau • glycerin • neopentyl glycol diheptanoate • polyester-8 • dimethicone • sorbitan stearate • butyloctyl salicylate • polysorbate 60 • butylene glycol • sodium acrylates copolymer • niacinamide • sodium hyaluronate • acetyl carnitine hcl • creatine • brassica oleracea gemmifera (brussels sprouts) extract • vaccinium angustifolium (blueberry) fruit extract • brassica oleracea italica (broccoli) extract • daucus carota sativa (carrot) root extract • brassica oleracea acephala (kale) leaf extract • spinacia oleracea (spinach) leaf extract • albizia julibrissin bark extract • cucumis sativus (cucumber) fruit extract • vaccinium macrocarpon (cranberry) fruit extract • plankton extract • laminaria saccharina extract • caffeine • adenosine phosphate • sea whip extract • yeast extract\faex\extrait de levure • sodium rna • phytic acid • lactobacillus ferment • algae extract • hordeum vulgare (barley) extract\extrait d'orge • silica • resveratrol • cetyl alcohol • tocopheryl acetate • sigesbeckia orientalis (st. paul's wort) extract • pentylene glycol • trehalose • styrene/acrylates copolymer • lecithin • helianthus annuus (sunflower) seedcake • micrococcus lysate • arabidopsis thaliana extract • biosaccharide gum-4 • ergothioneine • oryza sativa (rice) bran extract • capryloyl glycine • salicylic acid • isohexadecane • peg-8 laurate • polysorbate 80 • ethylhexylglycerin • propylene glycol dicaprate • 7-dehydrocholesterol • peg-100 stearate • acrylamide/sodium acryloyldimethyltaurate copolymer • tetrahexyldecyl ascorbate • propylene glycol caprylate • polyethylene • disodium edta • bht • phenoxyethanol • chlorphenesin • mica • titanium dioxide (ci 77891) [iln44783]

Other information

protect the product in this container from excessive heat and direct sun

PRINCIPAL DISPLAY PANEL - 48 ml Bottle Carton

CLINIQUE
FOR MEN

super
energizer

anti-fatigue
hydrating concentrate
broad spectrum
SPF 25

UVA/B + IR + BLUE LIGHT DEFENSE

1.6 FL.OZ.LIQ./48 ml e